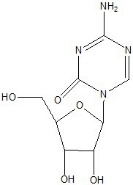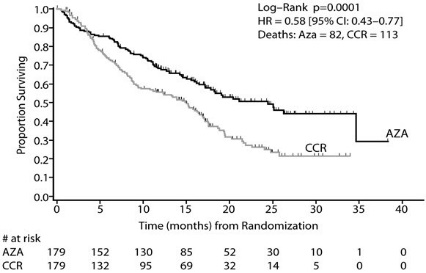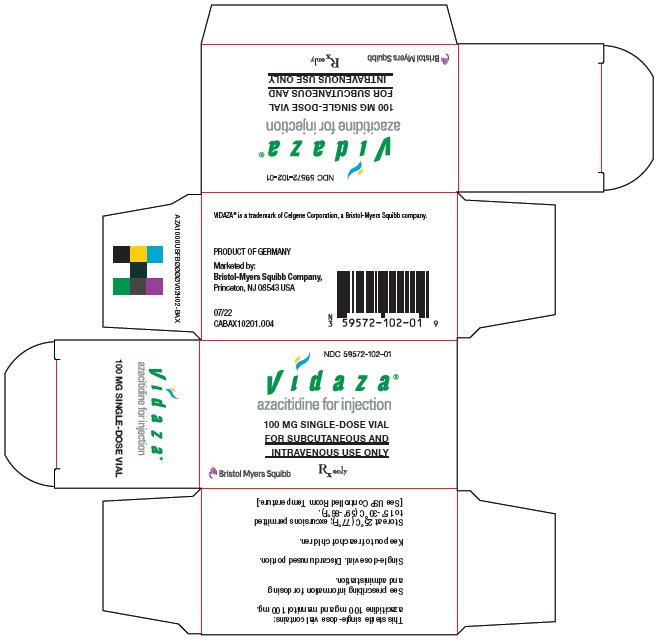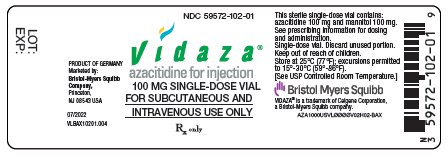 DRUG LABEL: VIDAZA
NDC: 59572-102 | Form: INJECTION, POWDER, LYOPHILIZED, FOR SOLUTION
Manufacturer: Celgene Corporation
Category: prescription | Type: HUMAN PRESCRIPTION DRUG LABEL
Date: 20240129

ACTIVE INGREDIENTS: AZACITIDINE 100 mg/1 1

HIGHLIGHTS OF PRESCRIBING INFORMATION

These highlights do not include all the information needed to use VIDAZA safely and effectively. See full prescribing information for VIDAZA.
VIDAZA (azacitidine for injection), for subcutaneous or intravenous use
Initial U.S. Approval: 2004

1 INDICATIONS AND USAGE

VIDAZA is a nucleoside metabolic inhibitor indicated for the treatment of:

- Adult patients with the following FAB myelodysplastic syndrome (MDS) subtypes: Refractory anemia (RA) or refractory anemia with ringed sideroblasts (RARS) (if accompanied by neutropenia or thrombocytopenia or requiring transfusions), refractory anemia with excess blasts (RAEB), refractory anemia with excess blasts in transformation (RAEB-T), and chronic myelomonocytic leukemia (CMMoL). (1.1)
- Pediatric patients aged 1 month and older with newly diagnosed Juvenile Myelomonocytic Leukemia (JMML). (1.2)

2 DOSAGE AND ADMINISTRATION

- Do not substitute VIDAZA for oral azacitidine. The indications and dosing regimen for VIDAZA differ from that of oral azacitidine (2.1, 5.1).
- MDS: The recommended starting dosage for the first treatment cycle, for all patients regardless of baseline hematology values, is VIDAZA 75 mg/m^2 daily for 7 days to be administered by subcutaneous injection or intravenous infusion. See full prescribing information for schedule for subsequent cycles. Premedicate for nausea and vomiting (2.2).
- JMML: See full prescribing information for recommended dosage and schedule.
- Continue treatment as long as the patient continues to benefit; up to 6 cycles for pediatric patients with JMML (2.3, 2.4).
- Monitor all patients for hematologic response and for renal toxicity; delay or reduce dosage as appropriate (2.3, 2.4, 2.6, 2.7).

3 DOSAGE FORMS AND STRENGTHS

- Lyophilized powder in 100 mg single-dose vials (3).

4 CONTRAINDICATIONS

- Advanced Malignant Hepatic Tumors (4.1).
- Hypersensitivity to Azacitidine or Mannitol (4.2).

5 WARNINGS AND PRECAUTIONS

- Risks of Substitution with Other Azacitidine Products: Do not substitute VIDAZA for oral azacitidine (2.1, 5.1).
- Anemia, Neutropenia and Thrombocytopenia: Monitor complete blood counts (CBC) frequently (5.2).
- Hepatotoxicity: Patients with severe preexisting hepatic impairment are at higher risk for toxicity (5.3).
- Renal Toxicity: Monitor patients with renal impairment for toxicity since azacitidine and its metabolites are primarily excreted by the kidneys (5.4).
- Tumor Lysis Syndrome: VIDAZA may cause fatal or serious tumor lysis syndrome, including in patients with MDS. Assess baseline risk and monitor and treat as appropriate (5.5).
- Embryo-Fetal Toxicity: VIDAZA can cause fetal harm. Advise female patients and male patients with female partners of reproductive potential of the potential risk to a fetus and to use effective contraception (5.6).

6 ADVERSE REACTIONS

Most common adverse reactions (>30%) in adult patients with MDS by subcutaneous route are: nausea, anemia, thrombocytopenia, vomiting, pyrexia, leukopenia, diarrhea, injection site erythema, constipation, neutropenia and ecchymosis. Most common adverse reactions by intravenous route also included petechiae, rigors, weakness and hypokalemia (6.1).

Most common adverse reactions (>30%) by intravenous route in pediatric patients with JMML are pyrexia, rash, upper respiratory tract infection, and anemia (6.1).

To report SUSPECTED ADVERSE REACTIONS, contact Bristol-Myers Squibb at 1-800-721-5072 or FDA at 1-800-FDA-1088 or www.fda.gov/medwatch.

8 USE IN SPECIFIC POPULATIONS

- Lactation: Advise not to breastfeed (8.2).

FULL PRESCRIBING INFORMATION

1 INDICATIONS AND USAGE

1.1 Myelodysplastic Syndromes (MDS)

VIDAZA® is indicated for treatment of adult patients with the following French-American-British (FAB) myelodysplastic syndrome subtypes: refractory anemia (RA) or refractory anemia with ringed sideroblasts (if accompanied by neutropenia or thrombocytopenia or requiring transfusions), refractory anemia with excess blasts (RAEB), refractory anemia with excess blasts in transformation (RAEB-T), and chronic myelomonocytic leukemia (CMMoL).

1.2 Juvenile Myelomonocytic Leukemia (JMML)

VIDAZA is indicated for the treatment of pediatric patients aged one month and older with newly diagnosed JMML.

2 DOSAGE AND ADMINISTRATION

2.1 Important Administration Information

Do not substitute VIDAZA for oral azacitidine. The indications and dosing regimen for VIDAZA differ from that of oral azacitidine [see Warnings and Precautions (5.1)].

2.2 First Treatment Cycle for Adults

The recommended starting dose for the first treatment cycle, for all patients regardless of baseline hematology laboratory values, is 75 mg/m^2 subcutaneously or intravenously, daily for 7 days. Premedicate patients for nausea and vomiting.

Obtain complete blood counts, liver chemistries and serum creatinine prior to the first dose.

2.3 Subsequent Treatment Cycles for Adults

Repeat cycles every 4 weeks. The dose may be increased to 100 mg/m^2 if no beneficial effect is seen after 2 treatment cycles and if no toxicity other than nausea and vomiting has occurred. It is recommended that patients be treated for a minimum of 4 to 6 cycles. However, complete or partial response may require additional treatment cycles. Treatment may be continued as long as the patient continues to benefit.

Monitor patients for hematologic response and renal toxicities [see Warnings and Precautions (5.4)], and delay or reduce dosage if necessary [see Dosage and Administration (2.6)].

2.4 Pediatric Patients with JMML

Table 1: Dosage and Administration for Pediatric Patients (JMML)

Pediatric Patients with JMML | Recommended Dose
Age 1 month to less than 1 year OR; weighing less than 10 kg | 2.5 mg/kg
Age 1 year and older AND weighing 10 kg; or greater | 75 mg/m^2

The recommended dosage for pediatric patients with JMML is provided in Table 1. VIDAZA is administered as an intravenous infusion daily for 7 days in a 28-day cycle. Patients should be treated for a minimum of 3 cycles and maximum of 6 cycles.

A delay in dose not exceeding 14 days can be considered for non-hematologic toxicities.

Monitor patients for hematologic response and renal toxicities [see Warnings and Precautions (5.4)], and delay or reduce dosage if necessary. Treatment may be continued up to six cycles as long as the patient continues to benefit.

2.5 Dosage Adjustment Based on Hematology Laboratory Values

- For adult patients with baseline (start of treatment) WBC greater than or equal to 3 x10^9/L, ANC greater than or equal to 1.5 x10^9/L, and platelets greater than or equal to 75 x10^9/L, adjust the dose as follows, based on nadir counts for any given cycle:

Nadir Counts |  | % Dose in the Next Course
ANC (x10^9/L) Less than 0.5 0.5 –1.5 Greater than 1.5 | Platelets (x10^9/L) Less than 25 25-50 Greater than 50 | 50% 67% 100%

- For adult patients whose baseline counts are WBC less than 3 x10^9/L, ANC less than 1.5 x10^9/L, or platelets less than 75 x10^9/L, base dose adjustments on nadir counts and bone marrow biopsy cellularity at the time of the nadir as noted below, unless there is clear improvement in differentiation (percentage of mature granulocytes is higher and ANC is higher than at onset of that course) at the time of the next cycle, in which case continue the current dose.

WBC or Platelet Nadir % decrease in counts from baseline | Bone Marrow Biopsy Cellularity at Time of Nadir (%)
WBC or Platelet Nadir % decrease in counts from baseline | 30-60 | 15-30 | Less than 15
 | % Dose in the Next Course
50 - 75 | 100 | 50 | 33
Greater than 75 | 75 | 50 | 33

If a nadir as defined in the table above has occurred, give the next course 28 days after the start of the preceding course, provided that both the WBC and the platelet counts are greater than 25% above the nadir and rising. If a greater than 25% increase above the nadir is not seen by day 28, reassess counts every 7 days. If a 25% increase is not seen by day 42, reduce the scheduled dose by 50%.

Pediatric Patients with JMML

As hematological toxicity will be difficult to assess and to differentiate from the natural course of the underlying disorder, dose reductions are not recommended due to hematological toxicity within the first 3 cycles. However, if the patient has a neutrophil count of less than 0.5 x10^9/L at end of Cycle 3 or on Day 1 of Cycles 5 or 6, discontinue the treatment.

2.6 Dosage Adjustment Based on Serum Electrolytes and Renal Toxicity

If unexplained reductions in serum bicarbonate levels to less than 20 mEq/L occur, reduce the dosage by 50% for the next course. Similarly, if unexplained elevations of BUN or serum creatinine occur, delay the next cycle until values return to normal or baseline and reduce the dose by 50% for the next course [see Warnings and Precautions (5.4)].

2.7 Use in Geriatric Patients

Azacitidine and its metabolites are known to be substantially excreted by the kidney, and the risk of toxic reactions to this drug may be greater in patients with impaired renal function. Because elderly patients are more likely to have decreased renal function, select the dose carefully and monitor renal function [see Warnings and Precautions (5.4) and Use in Specific Populations (8.5)].

2.8 Preparation of VIDAZA

VIDAZA is a hazardous drug. Follow applicable special handling and disposal procedures.

The VIDAZA vial is single-dose and does not contain any preservatives. Discard unused portions of each vial properly [see How Supplied/Storage and Handling (16)]. Do not save any unused portions for later administration.

2.9 Instructions for Subcutaneous Administration

Reconstitute VIDAZA aseptically with 4 mL Sterile Water for Injection, USP to obtain a concentration of 25 mg/mL. Inject the diluent slowly into the vial. Vigorously shake or roll the vial until a uniform suspension is achieved. The suspension will be cloudy. Do not filter the suspension after reconstitution. Doing so could remove the active substance.

Preparation for Immediate Subcutaneous Administration: For doses requiring more than 1 vial, divide the dose equally between the syringes (e.g., dose 150 mg = 6 mL, 2 syringes with 3 mL in each syringe) and inject into two separate sites. Due to retention in the vial and needle, it may not be feasible to withdraw all of the suspension from the vial. The product may be held at room temperature for up to 1 hour, but must be administered within 1 hour after reconstitution.

Preparation for Delayed Subcutaneous Administration: The reconstituted product may be kept in the vial or drawn into a syringe. For doses requiring more than 1 vial, divide the dose equally between the syringes (e.g., dose 150 mg = 6 mL, 2 syringes with 3 mL in each syringe) and inject into two separate sites. Due to retention in the vial and needle, it may not be feasible to withdraw all of the suspension from the vial. The product must be refrigerated immediately. See Table 2 for suspension stability storage timelines based on the temperature of the diluent for delayed subcutaneous administration.

After removal from refrigerated conditions, the suspension may be allowed to equilibrate to room temperature for up to 30 minutes prior to administration.

Subcutaneous Administration

To provide a homogeneous suspension, the contents of the dosing syringe must be re-suspended immediately prior to administration. To re-suspend, vigorously roll the syringe between the palms until a uniform, cloudy suspension is achieved.

VIDAZA suspension is administered subcutaneously. Rotate sites for each injection (thigh, abdomen, or upper arm). New injections should be given at least one inch from an old site and never into areas where the site is tender, bruised, red, or hard.

Table 2 Suspension Stability: Storage timelines based on the temperature of the diluent for suspension stability storage:

Suspension Stability Storage timelines
Diluent | Storage; Temperature/Duration
Room temperature (25°C / 77°F); Sterile Water for Injection, USP | Store at room; temperature at 25°C; (77°F) for up to 1 hour; or refrigerated at 2°C to; 8°C (36°F to 46°F) for; up to 8 hours.
Cold (2°C to 8°C / 36°F to 46°F); Sterile Water for Injection, USP | Store refrigerated at; 2°C to 8°C; (36°F to 46°F) for up to; 22 hours.

2.10 Instructions for Intravenous Administration

Parenteral drug product should be inspected visually for particulate matter and discoloration prior to administration, whenever solution and container permit. Do not use the product if there is evidence of particulate matter or discoloration.

Adult Patients with MDS

Reconstitute the appropriate number of VIDAZA vials to achieve the desired dose. Reconstitute each vial with 10 mL Sterile Water for Injection, USP. Vigorously shake or roll the vial until all solids are dissolved. The resulting solution will contain azacitidine 10 mg/mL. The solution should be clear.

Withdraw the required amount of VIDAZA solution to deliver the desired dose and inject into a 50 -100 mL infusion bag of either 0.9% Sodium Chloride Injection, USP or Lactated Ringer’s Injection, USP.

Pediatric Patients with JMML

For pediatric patients with JMML, withdraw the required amount of VIDAZA solution to deliver the desired dose and inject into an infusion bag (volume up to 100 mL) of either 0.9% Sodium Chloride Injection, USP or Lactated Ringer’s Injection, USP to achieve a final VIDAZA concentration between 0.9 mg/mL and 4 mg/mL.

Intravenous Solution Incompatibility

VIDAZA is incompatible with 5% Dextrose Injection, USP solutions, Hespan, or solutions that contain bicarbonate. These solutions have the potential to increase the rate of degradation of VIDAZA and should therefore be avoided.

Intravenous Administration

VIDAZA solution is administered intravenously. Administer the total dose over a period of 10 - 40 minutes. The administration must be completed within 1 hour of reconstitution of the VIDAZA vial.

Solution Stability: VIDAZA reconstituted and diluted for intravenous administration may be stored at 25°C (77°F), but administration must be completed within 1 hour of reconstitution.

3 DOSAGE FORMS AND STRENGTHS

VIDAZA (azacitidine for injection) is supplied as lyophilized powder in 100 mg single-dose vials.

4 CONTRAINDICATIONS

4.1 Advanced Malignant Hepatic Tumors

VIDAZA is contraindicated in patients with advanced malignant hepatic tumors [see Warnings and Precautions (5.3)].

4.2 Hypersensitivity to Azacitidine or Mannitol

VIDAZA is contraindicated in patients with a known hypersensitivity to azacitidine or mannitol.

5 WARNINGS AND PRECAUTIONS

5.1 Risks of Substitution with Other Azacitidine Products

Due to substantial differences in the pharmacokinetic parameters [see Clinical Pharmacology (12.3)], the recommended dose and schedule for VIDAZA are different from those of oral azacitidine products. Treatment of patients using VIDAZA at the recommended dosage of oral azacitidine may result in a fatal adverse reaction. Treatment of patients using oral azacitidine at the doses recommended for VIDAZA may not be effective.

Do not substitute VIDAZA for oral azacitidine [see Dosage and Administration (2.1)].

5.2 Anemia, Neutropenia and Thrombocytopenia

VIDAZA causes anemia, neutropenia and thrombocytopenia in adult patients with MDS and in pediatric patients with JMML. Monitor complete blood counts frequently for response and/or toxicity, at a minimum, prior to each dosing cycle.

In adult patients with MDS, after administration of the recommended dosage for the first cycle, adjust dosage for subsequent cycles based on nadir counts and hematologic response [see Dosage and Administration (2.5)].

In pediatric patients with JMML, dose reductions due to hematological toxicity are not recommended within the first 3 cycles as hematological toxicity will be difficult to assess and to differentiate from the natural course of the underlying disorder [see Dosage and Administration (2.5)].

5.3 Hepatotoxicity in Patients with Severe Pre-existing Hepatic Impairment

Because azacitidine is potentially hepatotoxic in patients with severe pre-existing hepatic impairment, caution is needed in patients with liver disease. Patients with extensive tumor burden due to metastatic disease have been reported to experience progressive hepatic coma and death during azacitidine treatment, especially in such patients with baseline albumin <30 g/L. Azacitidine is contraindicated in patients with advanced malignant hepatic tumors [see Contraindications (4.1)]. Monitor liver chemistries prior to initiation of therapy and with each cycle.

Safety and effectiveness of VIDAZA in patients with MDS or in pediatric patients with JMML and hepatic impairment have not been studied as these patients were excluded from the clinical trials.

5.4 Renal Toxicity

Renal toxicity ranging from elevated serum creatinine to renal failure and death have been reported in patients treated with intravenous azacitidine in combination with other chemotherapeutic agents for non-MDS conditions. In addition, renal tubular acidosis, defined as a fall in serum bicarbonate to <20 mEq/L in association with an alkaline urine and hypokalemia (serum potassium <3 mEq/L) developed in 5 patients with CML treated with azacitidine and etoposide. Monitor serum creatinine and electrolytes prior to initiation of therapy and with each cycle. If unexplained reductions in serum bicarbonate <20 mEq/L or elevations of BUN or serum creatinine occur, reduce or hold the dose [see Dosage and Administration (2.6)].

Patients with renal impairment may be at increased risk for renal toxicity. Also, azacitidine and its metabolites are primarily excreted by the kidney. Therefore, monitor these patients closely for toxicity [see Dosage and Administration (2.6, 2.7)]. Patients with MDS or pediatric patients with JMML and renal impairment were excluded from the clinical studies.

5.5 Tumor Lysis Syndrome

VIDAZA may cause fatal or serious tumor lysis syndrome, including in patients with MDS. Tumor lysis syndrome may occur despite concomitant use of allopurinol. Assess baseline risk and monitor and treat as appropriate.

5.6 Embryo-Fetal Toxicity

Based on the mechanism of action and findings in animals, VIDAZA can cause fetal harm when administered to a pregnant woman. Azacitidine administered to pregnant rats via a single intraperitoneal (IP) dose approximating 8% of the recommended human daily dose caused fetal death and anomalies.

Advise pregnant women of the potential risk to a fetus. Advise females of reproductive potential to use effective contraception during treatment with VIDAZA and for 6 months after the last dose. Advise males with female partners of reproductive potential to use effective contraception during treatment with VIDAZA and for 3 months after the last dose [see Use in Specific Populations (8.1, 8.3)].

6 ADVERSE REACTIONS

The following adverse reactions are described in other labeling sections:

- Anemia, Neutropenia and Thrombocytopenia [see Warnings and Precautions (5.2)]
- Hepatotoxicity in Patients with Severe Pre-existing Hepatic Impairment [see Warnings and Precautions (5.3)]
- Renal Toxicity [see Warnings and Precautions (5.4)]
- Tumor Lysis Syndrome [see Warnings and Precautions (5.5)]

6.1 Clinical Trials Experience

Because clinical trials are conducted under widely varying conditions, adverse reaction rates observed in the clinical trials of a drug cannot be directly compared to rates in the clinical trials of another drug and may not reflect the rates observed in practice.

MDS

The data described below reflect exposure to VIDAZA in 443 patients with MDS from 4 clinical studies. Study 1 was a supportive-care controlled trial (subcutaneous administration), Studies 2 and 3 were single arm studies (one with subcutaneous administration and one with intravenous administration), and Study 4 was an international randomized trial (subcutaneous administration) [see Clinical Studies (14.1)].

In Studies 1, 2 and 3, a total of 268 patients were exposed to VIDAZA, including 116 exposed for 6 cycles (approximately 6 months) or more and 60 exposed for greater than 12 cycles (approximately one year). VIDAZA was studied primarily in supportive-care controlled and uncontrolled trials (n=150 and n=118, respectively). The population in the subcutaneous studies (n=220) was 23 to 92 years old (mean 66.4 years), 68% male, and 94% white, and had MDS or AML. The population in the intravenous study (n=48) was 35 to 81 years old (mean 63.1 years), 65% male, and 100% white. Most patients received average daily doses between 50 and 100 mg/m^2.

In Study 4, a total of 175 patients with higher-risk MDS (primarily RAEB and RAEB-T subtypes) were exposed to VIDAZA. Of these patients, 119 were exposed for 6 or more cycles, and 63 for at least 12 cycles. The mean age of this population was 68.1 years (ranging from 42 to 83 years), 74% were male, and 99% were white. Most patients received daily VIDAZA doses of 75 mg/m^2.

Most Commonly Occurring Adverse Reactions (Subcutaneous or Intravenous Route) in Adult Patients with MDS: nausea, anemia, thrombocytopenia, vomiting, pyrexia, leukopenia, diarrhea, injection site erythema, constipation, neutropenia, ecchymosis. The most common adverse reactions by intravenous route also included petechiae, rigors, weakness and hypokalemia.

Adverse Reactions Most Frequently (>2%) Resulting in Clinical Intervention (Subcutaneous or Intravenous Route) in Adult Patients with MDS:

Discontinuation: leukopenia, thrombocytopenia, neutropenia.

Dose Held: leukopenia, neutropenia, thrombocytopenia, pyrexia, pneumonia, febrile neutropenia.

Dose Reduced: leukopenia, neutropenia, thrombocytopenia.

Table 3 presents adverse reactions occurring in at least 5% of patients treated with VIDAZA (subcutaneous) in Studies 1 and 2. It is important to note that duration of exposure was longer for the VIDAZA-treated group than for the observation group: patients received VIDAZA for a mean of 11.4 months while mean time in the observation arm was 6.1 months.

Table 3: Most Frequently Observed Adverse Reactions (≥ 5% in All Subcutaneous VIDAZA Treated Patients; Studies 1 and 2)
 | Number (%) of Patients
System Organ Class Preferred Terma | All VIDAZAb (N=220) | Observationc (N=92)
Blood and lymphatic system disorders
Anemia | 153 (70) | 59 (64)
Anemia aggravated | 12 (6) | 5 (5)
Febrile neutropenia | 36 (16) | 4 (4)
Leukopenia | 106 (48) | 27 (29)
Neutropenia | 71 (32) | 10 (11)
Thrombocytopenia | 144 (66) | 42 (46)
Gastrointestinal disorders
Abdominal tenderness | 26 (12) | 1 (1)
Constipation | 74 (34) | 6 (7)
Diarrhea | 80 (36) | 13 (14)
Gingival bleeding | 21 (10) | 4 (4)
Loose stools | 12 (6) | 0
Mouth hemorrhage | 11 (5) | 1 (1)
Nausea | 155 (71) | 16 (17)
Stomatitis | 17 (8) | 0
Vomiting | 119 (54) | 5 (5)
General disorders and administration site conditions
Chest pain | 36 (16) | 5 (5)
Injection site bruising | 31 (14) | 0
Injection site erythema | 77 (35) | 0
Injection site granuloma | 11 (5) | 0
Injection site pain | 50 (23) | 0
Injection site pigmentation changes | 11 (5) | 0
Injection site pruritus | 15 (7) | 0
Injection site reaction | 30 (14) | 0
Injection site swelling | 11 (5) | 0
Lethargy | 17 (8) | 2 (2)
Malaise | 24 (11) | 1 (1)
Pyrexia | 114 (52) | 28 (30)
Infections and infestations
Nasopharyngitis | 32 (15) | 3 (3)
Pneumonia | 24 (11) | 5 (5)
Upper respiratory tract infection | 28 (13) | 4 (4)
Injury, poisoning, and procedural complications
Post procedural hemorrhage | 13 (6) | 1 (1)
Metabolism and nutrition disorders
Anorexia | 45 (21) | 6 (7)
Musculoskeletal and connective tissue disorders
Arthralgia | 49 (22) | 3 (3)
Chest wall pain | 11 (5) | 0
Myalgia | 35 (16) | 2 (2)
Nervous system disorders
Dizziness | 41 (19) | 5 (5)
Headache | 48 (22) | 10 (11)
Psychiatric disorders
Anxiety | 29 (13) | 3 (3)
Insomnia | 24 (11) | 4 (4)
Respiratory, thoracic and mediastinal disorders
Dyspnea | 64 (29) | 11 (12)
Skin and subcutaneous tissue disorders
Dry skin | 11 (5) | 1 (1)
Ecchymosis | 67 (31) | 14 (15)
Erythema | 37 (17) | 4 (4)
Rash | 31 (14) | 9 (10)
Skin nodule | 11 (5) | 1 (1)
Urticaria | 13 (6) | 1 (1)
Vascular disorders
Hematoma | 19 (9) | 0
Hypotension | 15 (7) | 2 (2)
Petechiae | 52 (24) | 8 (9)
a Multiple terms of the same preferred terms for a patient are only counted once within each treatment group.
b Includes adverse reactions from all patients exposed to VIDAZA, including patients after crossing over from observations.
c Includes adverse reactions from observation period only; excludes any adverse events after crossover to VIDAZA.

Table 4 presents adverse reactions occurring in at least 5% of patients treated with VIDAZA in Study 4. Similar to Studies 1 and 2 described above, duration of exposure to treatment with VIDAZA was longer (mean 12.2 months) compared with best supportive care (mean 7.5 months).

Table 4: Most Frequently Observed Adverse Reactions (≥ 5% in the VIDAZA Treated Patients and the Percentage with NCI CTC Grade 3/4 Reactions; Study 4)
 | Number (%) of Patients
 | Any Grade |  | Grade 3/4
System Organ Class Preferred Terma | VIDAZA (N=175) | Best Supportive Care Only (N=102) | VIDAZA (N=175) | Best Supportive Care Only (N=102)
Blood and lymphatic system disorders
Anemia | 90 (51) | 45 (44) | 24 (14) | 9 (9)
Febrile neutropenia | 24 (14) | 10 (10) | 22 (13) | 7 (7)
Leukopenia | 32 (18) | 2 (2) | 26 (15) | 1 (1)
Neutropenia | 115 (66) | 29 (28) | 107 (61) | 22 (22)
Thrombocytopenia | 122 (70) | 35 (34) | 102 (58) | 29 (28)
Gastrointestinal disorders
Abdominal pain | 22 (13) | 7 (7) | 7 (4) | 0
Constipation | 88 (50) | 8 (8) | 2 (1) | 0
Dyspepsia | 10 (6) | 2 (2) | 0 | 0
Nausea | 84 (48) | 12 (12) | 3 (2) | 0
Vomiting | 47 (27) | 7 (7) | 0 | 0
General disorders and administration site conditions
Fatigue | 42 (24) | 12 (12) | 6 (3) | 2 (2)
Injection site bruising | 9 (5) | 0 | 0 | 0
Injection site erythema | 75 (43) | 0 | 0 | 0
Injection site hematoma | 11 (6) | 0 | 0 | 0
Injection site induration | 9 (5) | 0 | 0 | 0
Injection site pain | 33 (19) | 0 | 0 | 0
Injection site rash | 10 (6) | 0 | 0 | 0
Injection site reaction | 51 (29) | 0 | 1 (1) | 0
Pyrexia | 53 (30) | 18 (18) | 8 (5) | 1 (1)
Infections and infestations
Rhinitis | 10 (6) | 1 (1) | 0 | 0
Upper respiratory tract infection | 16 (9) | 4 (4) | 3 (2) | 0
Urinary tract infection | 15 (9) | 3 (3) | 3 (2) | 0
Investigations
Weight decreased | 14 (8) | 0 | 1 (1) | 0
Metabolism and nutrition disorders
Hypokalemia | 11 (6) | 3 (3) | 3 (2) | 3 (3)
Nervous system disorders
Lethargy | 13 (7) | 2 (2) | 0 | 1 (1)
Psychiatric disorders
Anxiety | 9 (5) | 1 (1) | 0 | 0
Insomnia | 15 (9) | 3 (3) | 0 | 0
Renal and urinary disorders
Hematuria | 11 (6) | 2 (2) | 4 (2) | 1 (1)
Respiratory, thoracic and mediastinal disorders
Dyspnea | 26 (15) | 5 (5) | 6 (3) | 2 (2)
Dyspnea exertional | 9 (5) | 1 (1) | 0 | 0
Pharyngolaryngeal pain | 11 (6) | 3 (3) | 0 | 0
Skin and subcutaneous tissue disorders
Erythema | 13 (7) | 3 (3) | 0 | 0
Petechiae | 20 (11) | 4 (4) | 2 (1) | 0
Pruritus | 21 (12) | 2 (2) | 0 | 0
Rash | 18 (10) | 1 (1) | 0 | 0
Vascular disorders
Hypertension | 15 (9) | 4 (4) | 2 (1) | 2 (2)
a Multiple reports of the same preferred term from a patient were only counted once within each treatment.

In Studies 1, 2 and 4 with subcutaneous administration of VIDAZA, adverse reactions of neutropenia, thrombocytopenia, anemia, nausea, vomiting, diarrhea, constipation, and injection site erythema/reaction tended to increase in incidence with higher doses of VIDAZA. Adverse reactions that tended to be more pronounced during the first 1 to 2 cycles of subcutaneous treatment compared with later cycles included thrombocytopenia, neutropenia, anemia, nausea, vomiting, injection site erythema/pain/bruising/reaction, constipation, petechiae, dizziness, anxiety, hypokalemia, and insomnia. There did not appear to be any adverse reactions that increased in frequency over the course of treatment.

Overall, adverse reactions were qualitatively similar between the intravenous and subcutaneous studies. Adverse reactions that appeared to be specifically associated with the intravenous route of administration included infusion site reactions (e.g. erythema or pain) and catheter site reactions (e.g. infection, erythema, or hemorrhage).

In clinical studies of either subcutaneous or intravenous VIDAZA, the following serious adverse reactions occurring at a rate of <5% (and not described in Tables 2 or 3) were reported:

Blood and lymphatic system disorders: agranulocytosis, bone marrow failure, pancytopenia splenomegaly.

Cardiac disorders: atrial fibrillation, cardiac failure, cardiac failure congestive, cardio-respiratory arrest, congestive cardiomyopathy.

Eye disorders: eye hemorrhage

Gastrointestinal disorders: diverticulitis, gastrointestinal hemorrhage, melena, perirectal abscess.

General disorders and administration site conditions: catheter site hemorrhage, general physical health deterioration, systemic inflammatory response syndrome.

Hepatobiliary disorders: cholecystitis.

Immune system disorders: anaphylactic shock, hypersensitivity.

Infections and infestations: abscess limb, bacterial infection, cellulitis, blastomycosis, injection site infection, Klebsiella sepsis, neutropenic sepsis, pharyngitis streptococcal, pneumonia Klebsiella, sepsis, septic shock, Staphylococcal bacteremia, Staphylococcal infection, toxoplasmosis.

Metabolism and nutrition disorders: dehydration.

Musculoskeletal and connective tissue disorders: bone pain aggravated, muscle weakness, neck pain.

Neoplasms benign, malignant and unspecified: leukemia cutis.

Nervous system disorders: cerebral hemorrhage, convulsions, intracranial hemorrhage.

Renal and urinary disorders: loin pain, renal failure.

Respiratory, thoracic and mediastinal disorders: hemoptysis, lung infiltration, pneumonitis, respiratory distress.

Skin and subcutaneous tissue disorders: pyoderma gangrenosum, rash pruritic, skin induration.

Surgical and medical procedures: cholecystectomy.

Vascular disorders: orthostatic hypotension.

Juvenile Myelomonocytic Leukemia (JMML)

The safety of VIDAZA was evaluated in pediatric patients with JMML (N=18; 0.2-6.9 years old) in Study AZA-JMML-001 [see Clinical Studies (14.2)]. Patients received VIDAZA as intravenous infusion daily for 7 days in a 28-day cycle [see Dosage and Administration (2.4)].

Sixteen patients completed 3 cycles of therapy and 5 of the 16 patients completed 6 cycles. The median treatment duration was 12.3 weeks (range: 4.0 to 30.6 weeks) and the median total number of treatment cycles completed was 3 cycles (range: 1 to 6 cycles).

Serious adverse reactions occurred in 67% of patients who received VIDAZA for JMML.

Permanent discontinuation of VIDAZA due to an adverse reaction occurred in a single patient who had abdominal pain and acute respiratory distress syndrome.

The most common (≥30%) adverse reactions were pyrexia, rash, upper respiratory tract infection, and anemia.

Table 5 summarizes the adverse reactions in pediatric JMML.

Table 5: Most Frequently Observed Adverse Reactions (≥10%) in Pediatric Patients with JMML Receiving VIDAZA in Study AZA-JMML-001
Adverse Reaction | All Grades; N=18; % | Grade 3 or 4; N=18; %
General disorders and administration site conditions
Pyrexia | 61 | 0
Edemaa | 11 | 0
Skin and subcutaneous tissue disorders
Rashb | 44 | 0
Pruritusc | 22 | 0
Dermatitis allergic | 11 | 0
Petechiae | 11 | 0
Infections and infestations
Upper respiratory tract infectiond | 44 | 6
Febrile infection | 11 | 6
Fungal infectione | 11 | 6
Pneumoniaf | 11 | 0
Blood and lymphatic system disorders
Anemia | 39 | 33
Thrombocytopenia | 28 | 22
Neutropenia | 17 | 11
Febrile Neutropenia | 11 | 6
Lymphadenopathy | 11 | 6
Gastrointestinal disorders
Vomiting | 28 | 0
Abdominal paing | 22 | 11
Constipation | 22 | 0
Diarrhea | 22 | 6
Hemorrhageh | 11 | 0
Nausea | 11 | 0
Ascites | 11 | 6
Respiratory, thoracic and mediastinal disorders
Cough | 22 | 0
Epistaxis | 17 | 6
Metabolism and nutrition disorders
Hyperuricemia | 17 | 0
Fluid retention | 11 | 0
Musculoskeletal and connective tissue disorders
Musculoskeletal paini | 11 | 0

a Grouped term includes: face edema, generalized edema, edema peripheral.

b Grouped term includes: rash, rash macular, dermatitis bullous, rash maculo-papular, rash papular, rash pruritic.

c Grouped term includes: pruritis, pruritis generalized.

d Grouped term includes: influenza, nasopharyngitis, Parainfluenzae virus infection, respiratory tract infection, rhinitis, upper respiratory tract infection, and viral upper respiratory tract infection

e Grouped term includes: anal candidiasis, Candida infection, oral candidiasis.

f Grouped term includes: lung infection, pneumonia respiratory syncytial viral.

g Grouped term includes: abdominal pain, abdominal pain upper.

h Grouped term includes: mouth hemorrhage, rectal hemorrhage.

i Grouped term includes: back pain, musculoskeletal pain, non-cardiac chest pain, pain in extremity.

6.2 Postmarketing Experience

The following adverse reactions have been identified during postmarketing use of VIDAZA. Because these reactions are reported voluntarily from a population of uncertain size, it is not always possible to reliably estimate their frequency or establish a causal relationship to drug exposure.

‑ Interstitial lung disease
‑ Tumor lysis syndrome
‑ Injection site necrosis
‑ Sweet’s syndrome (acute febrile neutrophilic dermatosis)
‑ Necrotizing fasciitis (including fatal cases)
‑ Differentiation syndrome
‑ Pericardial effusion
‑ Pericarditis
‑ Cutaneous vasculitis

8 USE IN SPECIFIC POPULATIONS

8.1 Pregnancy

Risk Summary
Based on its mechanism of action and findings in animals, VIDAZA can cause fetal harm when administered to a pregnant woman [see Clinical Pharmacology (12.1)]. There are no data on the use of azacitidine in pregnant women. Azacitidine was teratogenic and caused embryo-fetal lethality in animals at doses lower than the recommended human daily dose (see Data). Advise pregnant women of the potential risk to the fetus.

The background rate of major birth defects and miscarriage is unknown for the indicated population. All pregnancies have a background risk of birth defect, loss, or other adverse outcomes. In the U.S. general population, the estimated background risk of major birth defects and miscarriage in clinically recognized pregnancies is 2%-4% and 15%-20%, respectively.

Data
Animal Data
Early embryotoxicity studies in mice revealed a 44% frequency of intrauterine embryonal death (increased resorption) after a single IP (intraperitoneal) injection of 6 mg/m^2 (approximately 8% of the recommended human daily dose on a mg/m^2 basis) azacitidine on gestation day 10. Developmental abnormalities in the brain have been detected in mice given azacitidine on or before gestation day 15 at doses of ~3-12 mg/m^2 (approximately 4%-16% the recommended human daily dose on a mg/m^2 basis).

In rats, azacitidine was clearly embryotoxic when given IP on gestation days 4-8 (postimplantation) at a dose of 6 mg/m^2 (approximately 8% of the recommended human daily dose on a mg/m^2 basis), although treatment in the preimplantation period (on gestation days 1-3) had no adverse effect on the embryos. Azacitidine caused multiple fetal abnormalities in rats after a single IP dose of 3 to 12 mg/m^2 (approximately 8% the recommended human daily dose on a mg/m^2 basis) given on gestation day 9, 10, 11 or 12. In this study azacitidine caused fetal death when administered at 3-12 mg/m^2 on gestation days 9 and 10; average live animals per litter was reduced to 9% of control at the highest dose on gestation day 9. Fetal anomalies included: CNS anomalies (exencephaly/encephalocele), limb anomalies (micromelia, club foot, syndactyly, oligodactyly), and others (micrognathia, gastroschisis, edema, and rib abnormalities).

8.2 Lactation

Risk Summary
There is no information regarding the presence of azacitidine in human milk, the effects of VIDAZA on the breastfed infant, or the effects of VIDAZA on milk production. Because many drugs are excreted in human milk and because of the potential for tumorigenicity shown for azacitidine in animal studies [see Nonclinical Toxicology (13.1)] and the potential for serious adverse reactions in nursing infants from VIDAZA, advise patients not to breastfeed during treatment with VIDAZA and for 1 week after the last dose.

8.3 Females and Males of Reproductive Potential

Based on its mechanism of action and findings in animals, VIDAZA can cause fetal harm when administered to a pregnant woman [see Use in Specific Populations (8.1)].

Pregnancy Testing
Verify the pregnancy status of females of reproductive potential prior to initiating VIDAZA.

Contraception
Females
Advise pregnant women of the potential risk to a fetus. Advise females of reproductive potential to use effective contraception during treatment with VIDAZA and for 6 months after the last dose.

Males
Advise males with female partners of reproductive potential to use effective contraception during treatment with VIDAZA and for 3 months after the last dose.

Infertility
Based on animal data, azacitidine could have an effect on male or female fertility [see Nonclinical Toxicology (13.1)].

8.4 Pediatric Use

Safety and effectiveness of VIDAZA in pediatric patients with MDS have not been established.

The safety and effectiveness of VIDAZA have been established in pediatric patients with newly diagnosed JMML aged 1 month and older and the information on this use is discussed throughout the labeling. The safety and effectiveness of VIDAZA have not been established in pediatric patients younger than 1 month old [see Clinical Studies (14.2)].

8.5 Geriatric Use

Of the total number of patients in Studies 1, 2 and 3, 62% were 65 years and older and 21% were 75 years and older. No overall differences in effectiveness were observed between these patients and younger patients. In addition, there were no relevant differences in the frequency of adverse reactions observed in patients 65 years and older compared to younger patients.

Of the 179 patients randomized to azacitidine in Study 4, 68% were 65 years and older and 21% were 75 years and older. Survival data for patients 65 years and older were consistent with overall survival results. The majority of adverse reactions occurred at similar frequencies in patients <65 years of age and patients 65 years of age and older.

Elderly patients are more likely to have decreased renal function. Monitor renal function in these patients [see Dosage and Administration (2.7) and Warnings and Precautions (5.4)].

10 OVERDOSAGE

One case of overdose with VIDAZA was reported during clinical trials. A patient experienced diarrhea, nausea, and vomiting after receiving a single intravenous dose of approximately 290 mg/m^2, almost 4 times the recommended starting dose. The events resolved without sequelae, and the correct dose was resumed the following day. In the event of overdosage, the patient should be monitored with appropriate blood counts and should receive supportive treatment, as necessary. There is no known specific antidote for VIDAZA overdosage.

11 DESCRIPTION

VIDAZA (azacitidine for injection) contains azacitidine, which is a nucleoside metabolic inhibitor. Azacitidine is

4-amino-1-β-D-ribofuranosyl-s-triazin-2(1H)-one. The structural formula is as follows:

The empirical formula is C8H12N4O5. The molecular weight is 244. Azacitidine is a white to off-white solid. Azacitidine was found to be insoluble in acetone, ethanol, and methyl ethyl ketone; slightly soluble in ethanol/water (50/50), propylene glycol, and polyethylene glycol; sparingly soluble in water, water saturated octanol, 5% dextrose in water, N-methyl-2-pyrrolidone, normal saline and 5% Tween 80 in water; and soluble in dimethylsulfoxide (DMSO).

The finished product is supplied in a sterile form for reconstitution as a suspension for subcutaneous injection or reconstitution as a solution with further dilution for intravenous infusion. Vials of VIDAZA contain 100 mg of azacitidine and 100 mg mannitol as a sterile lyophilized powder.

12 CLINICAL PHARMACOLOGY

12.1 Mechanism of Action

VIDAZA is a pyrimidine nucleoside analog of cytidine. VIDAZA is believed to exert its antineoplastic effects by causing hypomethylation of DNA and direct cytotoxicity on abnormal hematopoietic cells in the bone marrow. The concentration of azacitidine required for maximum inhibition of DNA methylation in vitro does not cause major suppression of DNA synthesis. Hypomethylation may restore normal function to genes that are critical for differentiation and proliferation. The cytotoxic effects of azacitidine cause the death of rapidly dividing cells, including cancer cells that are no longer responsive to normal growth control mechanisms. Non-proliferating cells are relatively insensitive to azacitidine.

12.2 Pharmacodynamics

In pediatric patients with JMML post azacitidine treatment (75 mg/m^2 or 2.5 mg/kg), reductions in genome-wide DNA methylation (global DNA methylation scores) were attained in bone marrow granulocytes during the first treatment cycle, confirming the DNA-hypomethylating activity of azacitidine.

12.3 Pharmacokinetics

The pharmacokinetics of azacitidine were studied in 6 adult patients with MDS following a single 75 mg/m^2 subcutaneous dose and a single 75 mg/m^2 intravenous dose.

Absorption

Azacitidine is rapidly absorbed after subcutaneous administration; the peak plasma azacitidine concentration of 750 ± 403 ng/ml occurred in 0.5 hour after subcutaneous administration.

Distribution

The bioavailability of subcutaneous azacitidine relative to intravenous azacitidine is approximately 89%, based on area under the curve. Mean volume of distribution following intravenous dosing is 76 ± 26 L. Mean apparent subcutaneous clearance is 167 ± 49 L/hour and mean half-life after subcutaneous administration is 41 ± 8 minutes. The AUC and Cmax of subcutaneous administration of azacitidine in 21 patients with cancer were approximately dose proportional within the 25 to 100 mg/m^2 dose range. Multiple dosing at the recommended dose-regimen does not result in drug accumulation with intravenous or subcutaneous administration.

Elimination

Metabolism

An in vitro study of azacitidine incubation in human liver fractions indicated that azacitidine is not metabolized by the cytochrome P450 (CYP) enzymes. Azacitidine undergoes spontaneous hydrolysis and deamination mediated by cytidine deaminase.

Excretion

Published studies indicate that urinary excretion is the primary route of elimination of azacitidine and its metabolites. Following intravenous administration of radioactive azacitidine to 5 cancer patients, the cumulative urinary excretion was 85% of the radioactive dose. Fecal excretion accounted for <1% of administered radioactivity over 3 days. Mean excretion of radioactivity in urine following subcutaneous administration of ^14C-azacitidine was 50%. The mean elimination half-lives of total radioactivity (azacitidine and its metabolites) were similar after intravenous and subcutaneous administrations, about 4 hours.

Specific Populations

The effects of hepatic impairment, gender, or race/ethnicity on the pharmacokinetics of intravenous and subcutaneous azacitidine have not been studied.

Pediatric Patients

Following intravenous administration of a 75 mg/m^2 or 2.5 mg/kg dose in pediatric patients with JMML, population pharmacokinetic analysis determined that azacitidine rapidly reached a geometric mean Cmax of 4510 ng/mL (CV%: 65.6%), and a geometric mean AUC0-24 of 1550 ng∙h/mL (CV%: 56.6%). The geometric mean t1/2 was 0.3 hours (CV%: 59.9%), and the geometric mean clearance was 21.8 L/h (CV%: 102.2%).

Population PK analysis of 6 adults and 34 pediatric patients did not identify any clinically meaningful differences in the pharmacokinetics of intravenous azacitidine according to sex (62.5% male), and tumor type (MDS, JMML, AML). Increased clearance was associated with increased baseline body weight (4.6 to 102 kg). BSA or body weight-based dosing resulted in consistent plasma azacitidine exposure in pediatric patients with JMML across the body weight range (4.6 to 18.5 kg) and age range (0.2 to 6.9 years).

Patients with Renal Impairment

In adult patients with cancer, the pharmacokinetics of azacitidine in 6 patients with normal renal function (CLcr >80 mL/min) and 6 patients with severe renal impairment (CLcr <30 mL/min) were compared following daily subcutaneous dosing (Days 1 through 5) at 75 mg/m^2/day. Severe renal impairment increased azacitidine exposure by approximately 70% after single and 41% after multiple subcutaneous administrations. This increase in exposure was not correlated with an increase in adverse events. The exposure was similar to exposure in patients with normal renal function receiving 100 mg/m^2.

Drug-Drug Interactions

No formal clinical drug interaction studies with azacitidine have been conducted.

In vitro Studies

Cytochrome P450 (CYP) Enzymes: An in vitro study at azacitidine concentrations up to 100 µM (IV Cmax = 10.6 µM) in human liver microsomes indicated that azacitidine does not cause any inhibition of CYP isoforms CYP1A2, CYP2B6, CYP2C8, CYP2C9, CYP2C19, CYP2D6, CYP3A4, or CYP2E1 at clinically achievable concentrations.

In vitro studies with human cultured hepatocytes indicate that azacitidine at concentrations of 1.0 μM to 100 μM does not induce CYP 1A2, 2C19, or 3A4/5.

Transporter Systems: An in vitro study with LLC-PK1 cells expressing P-glycoprotein (P-gp) indicated that azacitidine is not a substrate or inhibitor of P-gp.

Azacitidine does not inhibit, breast cancer resistance protein (BCRP), organic anion transporters (OAT) OAT1 and OAT3, organic anion transporting polypeptides (OATP) OATP1B1 and OATP1B3, or organic cation transporter (OCT) OCT2 at clinically relevant concentrations.

13 NONCLINICAL TOXICOLOGY

13.1 Carcinogenesis, Mutagenesis, Impairment of Fertility

The potential carcinogenicity of azacitidine was evaluated in mice and rats. Azacitidine induced tumors of the hematopoietic system in female mice at 2.2 mg/kg (6.6 mg/m^2, approximately 8% the recommended human daily dose on a mg/m^2 basis) administered IP three times per week for 52 weeks. An increased incidence of tumors in the lymphoreticular system, lung, mammary gland, and skin was seen in mice treated with azacitidine IP at 2.0 mg/kg (6.0 mg/m^2, approximately 8% the recommended human daily dose on a mg/m^2 basis) once a week for 50 weeks. A tumorigenicity study in rats dosed twice weekly at 15 or 60 mg/m^2 (approximately 20%-80% the recommended human daily dose on a mg/m^2 basis) revealed an increased incidence of testicular tumors compared with controls.

The mutagenic and clastogenic potential of azacitidine was tested in in vitro bacterial systems Salmonella typhimurium strains TA100 and several strains of trpE8, Escherichia coli strains WP14 Pro, WP3103P, WP3104P, and CC103; in in vitro forward gene mutation assay in mouse lymphoma cells and human lymphoblast cells; and in an in vitro micronucleus assay in mouse L5178Y lymphoma cells and Syrian hamster embryo cells. Azacitidine was mutagenic in bacterial and mammalian cell systems. The clastogenic effect of azacitidine was shown by the induction of micronuclei in L5178Y mouse cells and Syrian hamster embryo cells.

Administration of azacitidine to male mice at 9.9 mg/m^2 (approximately 9% the recommended human daily dose on a mg/m^2 basis) daily for 3 days prior to mating with untreated female mice resulted in decreased fertility and loss of offspring during subsequent embryonic and postnatal development. Treatment of male rats 3 times per week for 11 or 16 weeks at doses of 15-30 mg/m^2 (approximately 20%-40%, the recommended human daily dose on a mg/m^2 basis) resulted in decreased weight of the testes and epididymides, and decreased sperm counts accompanied by decreased pregnancy rates and increased loss of embryos in mated females. In a related study, male rats treated for 16 weeks at 24 mg/m^2 resulted in an increase in abnormal embryos in mated females when examined on day 2 of gestation.

14 CLINICAL STUDIES

14.1 Myelodysplastic Syndromes (MDS)

Study 1 was a randomized, open-label, controlled trial carried out in 53 U.S. sites compared the safety and efficacy of subcutaneous VIDAZA plus supportive care with supportive care alone (“observation”) in adult patients with any of the five FAB subtypes of myelodysplastic syndromes (MDS): refractory anemia (RA), RA with ringed sideroblasts (RARS), RA with excess blasts (RAEB), RAEB in transformation (RAEB-T), and chronic myelomonocytic leukemia (CMMoL). RA and RARS patients were included if they met one or more of the following criteria: required packed RBC transfusions; had platelet counts ≤50.0 x 10^9/L; required platelet transfusions; or were neutropenic (ANC <1.0 x 10^9/L) with infections requiring treatment with antibiotics. Patients with acute myelogenous leukemia (AML) were not intended to be included. Supportive care allowed in this study included blood transfusion products, antibiotics, antiemetics, analgesics and antipyretics. The use of hematopoietic growth factors was prohibited. Baseline patient and disease characteristics are summarized in Table 6; the 2 groups were similar.

VIDAZA was administered at a subcutaneous dose of 75 mg/m^2 daily for 7 days every 4 weeks. The dose was increased to 100 mg/m^2 if no beneficial effect was seen after 2 treatment cycles. The dose was decreased and/or delayed based on hematologic response or evidence of renal toxicity. Patients in the observation arm were allowed by protocol to cross over to VIDAZA if they had increases in bone marrow blasts, decreases in hemoglobin, increases in red cell transfusion requirements, or decreases in platelets, or if they required a platelet transfusion or developed a clinical infection requiring treatment with antibiotics. For purposes of assessing efficacy, the primary endpoint was response rate (as defined in Table 7).

Of the 191 patients included in the study, independent review (adjudicated diagnosis) found that 19 had the diagnosis of AML at baseline. These patients were excluded from the primary analysis of response rate, although they were included in an intent-to-treat (ITT) analysis of all patients randomized. Approximately 55% of the patients randomized to observation crossed over to receive VIDAZA treatment.

Table 6. Baseline Demographics and Disease Characteristics

 | VIDAZA (N=99) | Observation (N=92)
Gender (n%)
Male | 72 (72.7) | 60 (65.2)
Female | 27 (27.3) | 32 (34.8)
Race (n%)
White | 93 (93.9) | 85 (92.4)
Black | 1 (1.0) | 1 (1.1)
Hispanic | 3 (3.0) | 5 (5.4)
Asian/Oriental | 2 (2.0) | 1 (1.1)
Age (years)
N | 99 | 91
Mean ± SD | 67.3 ± 10.39 | 68.0 ± 10.23
Range | 31 - 92 | 35 - 88
Adjudicated MDS diagnosis at study entry (n%)
RA | 21 (21.2) | 18 (19.6)
RARS | 6 (6.1) | 5 (5.4)
RAEB | 38 (38.4) | 39 (42.4)
RAEB-T | 16 (16.2) | 14 (15.2)
CMMoL | 8 (8.1) | 7 (7.6)
AML | 10 (10.1) | 9 (9.8)
Transfusion product used in 3 months before study entry (n%)
Any transfusion product | 70 (70.7) | 59 (64.1)
Blood cells, packed human | 66 (66.7) | 55 (59.8)
Platelets, human blood | 15 (15.2) | 12 (13.0)
Hetastarch | 0 (0.0) | 1 (1.1)
Plasma protein fraction | 1 (1.0) | 0 (0.0)
Other | 2 (2.0) | 2 (2.2)

Table 7. Response Criteria

 |  | RA | RARS | RAEB | RAEB-T | CMMoL
Complete Response (CR), duration ≥4 weeks | Marrow | <5% blasts
Complete Response (CR), duration ≥4 weeks | Peripheral Blood | Normal CBC if abnormal at baseline Absence of blasts in the peripheral circulation
Partial Response (PR), duration ≥4 weeks | Marrow | No marrow requirements |  | ≥50% decrease in blasts Improvement of marrow dyspoiesis
Partial Response (PR), duration ≥4 weeks | Peripheral Blood | ≥50% restoration in the deficit from normal levels of baseline white cells, hemoglobin and platelets if abnormal at baseline No blasts in the peripheral circulation For CMMoL, if WBC is elevated at baseline, a ≥75% reduction in the excess count over the upper limit of normal

The overall response rate (CR + PR) of 15.7% in VIDAZA-treated patients without AML (16.2% for all VIDAZA randomized patients including AML) was statistically significantly higher than the response rate of 0% in the observation group (p<0.0001) (Table 8). The majority of patients who achieved either CR or PR had either 2 or 3 cell line abnormalities at baseline (79%; 11/14) and had elevated bone marrow blasts or were transfusion dependent at baseline. Patients responding to VIDAZA had a decrease in bone marrow blasts percentage, or an increase in platelets, hemoglobin or WBC. Greater than 90% of the responders initially demonstrated these changes by the 5th treatment cycle. All patients who had been transfusion dependent became transfusion independent during PR or CR. The mean and median duration of clinical response of PR or better was estimated as 512 and 330 days, respectively; 75% of the responding patients were still in PR or better at completion of treatment. Response occurred in all MDS subtypes as well as in patients with adjudicated baseline diagnosis of AML.

Table 8. Response Rates

 | VIDAZA (N=89) | Observation Before Crossover (N=83)
Response | n (%) | n (%) | P value
Overall (CR+PR) | 14 (15.7) | 0 (0.0) | (<0.0001)
Complete (CR) | 5 (5.6) | 0 (0.0) | (0.06)
Partial (PR) | 9 (10.1) | 0 (0.0) | --

Patients in the observation group who crossed over to receive VIDAZA treatment (47 patients) had a response rate of 12.8%.

Study 2, a multi-center, open-label, single-arm study of 72 patients with RAEB, RAEB-T, CMMoL, or AML was also carried out. Treatment with subcutaneous VIDAZA resulted in a response rate (CR + PR) of 13.9%, using criteria similar to those described above. The mean and median duration of clinical response of PR or better was estimated as 810 and 430 days, respectively; 80% of the responding patients were still in PR or better at the time of completion of study involvement. In Study 3, another open-label, single-arm study of 48 patients with RAEB, RAEB-T, or AML, treatment with intravenous VIDAZA resulted in a response rate of 18.8%, again using criteria similar to those described above. The mean and median duration of clinical response of PR or better was estimated as 389 and 281 days, respectively; 67% of the responding patients were still in PR or better at the time of completion of treatment. Response occurred in all MDS subtypes as well as in patients with adjudicated baseline diagnosis of AML in both of these studies. VIDAZA dosage regimens in these 2 studies were similar to the regimen used in the controlled study.

Benefit was seen in patients who did not meet the criteria for PR or better, but were considered “improved.” About 24% of VIDAZA-treated patients were considered improved, and about 2/3 of those lost transfusion dependence. In the observation group, only 5/83 patients met criteria for improvement; none lost transfusion dependence. In all 3 studies, about 19% of patients met criteria for improvement with a median duration of 195 days.

Study 4 was an international, multicenter, open-label, randomized trial in patients with MDS with RAEB, RAEB-T or modified CMMoL according to FAB classification and Intermediate-2 and High risk according to IPSS classification. Of the 358 patients enrolled in the study, 179 were randomized to receive azacitidine plus best supportive care (BSC) and 179 were randomized to receive conventional care regimens (CCR) plus BSC (105 to BSC alone, 49 to low dose cytarabine and 25 to chemotherapy with cytarabine and anthracycline). The primary efficacy endpoint was overall survival.

The azacitidine and CCR groups were comparable for baseline parameters. The median age of patients was 69 years (range was 38-88 years), 98% were Caucasian, and 70% were male. At baseline, 95% of the patients were higher risk by FAB classification: RAEB (58%), RAEB-T (34%), and CMMoL (3%). By IPSS classification, 87% were higher risk: Int-2 (41%), High (47%). At baseline, 32% of patients met WHO criteria for AML.

Azacitidine was administered subcutaneously at a dose of 75 mg/m^2 daily for 7 consecutive days every 28 days (which constituted one cycle of therapy). Patients continued treatment until disease progression, relapse after response, or unacceptable toxicity. Azacitidine patients were treated for a median of 9 cycles (range 1 to 39), BSC only patients for a median of 7 cycles (range 1 to 26), low dose cytarabine patients for a median of 4.5 cycles (range 1 to 15), and chemotherapy with cytarabine and anthracycline patients for a median of 1 cycle (range 1 to 3, i.e. induction plus 1 or 2 consolidation cycles).

In the Intent-to-Treat analysis, patients treated with azacitidine demonstrated a statistically significant difference in overall survival as compared to patients treated with CCR (median survival of 24.5 months vs. 15.0 months; stratified log-rank p=0.0001). The hazard ratio describing this treatment effect was 0.58 (95% CI: 0.43, 0.77).

Kaplan-Meier Curve of Time to Death from Any Cause: (Intent-to-Treat Population)

Key: AZA = azacitidine; CCR = conventional care regimens; CI = confidence interval; HR = Hazard Ratio

Azacitidine treatment led to a reduced need for red blood cell transfusions (see Table 8). In patients treated with azacitidine who were RBC transfusion dependent at baseline and became transfusion independent, the median duration of RBC transfusion independence was 13.0 months.

Table 9. Effect of Azacitidine on RBC Transfusions in Patients with MDS

Efficacy Parameter | Azacitidine plus BSC (n= 179) | Conventional Care Regimens (n= 179)
Number and percent of patients who were transfusion dependent at baseline who became transfusion independent on treatment^1 | 50/111 (45.0%) | 13/114 (11.4%)
 | (95% CI: 35.6%, 54.8%) | (95% CI: 6.2%, 18.7%)
Number and percent of patients who were transfusion-independent at baseline who became transfusion-dependent on treatment | 10/68 (14.7%) | 28/65 (43.1%)
Number and percent of patients who were transfusion-independent at baseline who became transfusion-dependent on treatment | (95% CI: 7.3%, 25.4%) | (95% CI: 30.9%, 56.0%)

^1A patient was considered RBC transfusion independent during the treatment period if the patient had no RBC transfusions during any 56 consecutive days or more during the treatment period. Otherwise, the patient was considered transfusion dependent.

14.2 Juvenile Myelomonocytic Leukemia (JMML)

AZA-JMML-001 (NCT02447666) was an international, multicenter, open-label study to evaluate the pharmacokinetics, pharmacodynamics, safety, and activity of VIDAZA prior to hematopoietic stem cell transplantation (HSCT) in a total of 18 pediatric patients (median age of 2.1 years, range 0.2-6.9 years; 61% male; 89% white) with juvenile myelomonocytic leukemia (JMML).

Patients with newly diagnosed JMML were included if they met the following criteria: diagnosis confirmed in peripheral blood and bone marrow, and had one of the following: somatic mutation in PTPN11, KRAS, or NRAS and HbF % > 5 x normal value for age, or clinical diagnosis of neurofibromatosis Type 1 (NF-1). Additionally, patients included had no CNS involvement, isolated extramedullary disease, or germline molecular aberrations in CBL, PTPN11, NRAS, or KRAS.

Eighteen patients with JMML (13 PTPN11, 3 NRAS, 1 KRAS somatic mutations and 1 clinical diagnosis of neurofibromatosis type 1 [NF 1]) were enrolled. Patients were treated with intravenous VIDAZA [see Dosage and Administration (2.4)], daily on Days 1 to 7 of a 28-day cycle for a minimum of 3 cycles and a maximum of 6 cycles, provided the patients did not have disease progression or were ready for HSCT between Cycles 4 and 6. The efficacy of VIDAZA was established based on clinical complete remission (cCR) or clinical partial remission (cPR) according to the International JMML response criteria at 3 months (Cycle 3 Day 28). Responses must have been sustained for at least 4 weeks either in the 4-week period preceding or succeeding Cycle 3 Day 28 (i.e., sustained over the period Cycle 2 Day 28 to Cycle 3 Day 28, or Cycle 3 Day 28 to Cycle 4 Day 28).

There were a total of 9 patients (50%, 95% CI 26-74) with a confirmed clinical response. Of these 9 patients, there were 3 cCR and 6 cPR. The median time to response was 1.2 months (range 1-1.9 months). The proportion of patients with JMML undergoing HSCT was 94% and the median time to HSCT was 4.6 months (range 2.8-19 months).

15 REFERENCES

1. “OSHA Hazardous Drugs.” OSHA. http://www.osha.gov/SLTC/hazardousdrugs/index.html

16 HOW SUPPLIED/STORAGE AND HANDLING

How Supplied

VIDAZA (azacitidine for injection) is supplied as a lyophilized powder in 100 mg single-dose vials packaged in cartons of 1 vial (NDC 59572-102-01).

Storage

Store unreconstituted vials at 25º C (77º F); excursions permitted to 15º-30º C (59º-86º F) (See USP Controlled Room Temperature).

Handling and Disposal

VIDAZA is a hazardous drug. Follow applicable special handling and disposal procedures.

17 PATIENT COUNSELING INFORMATION

Hepatotoxicity in Patients with Severe Pre-Existing Hepatic Impairment
Instruct patients to inform their physician about any underlying liver disease [see Warnings and Precautions (5.3)].

Renal Toxicity
Instruct patients to inform their physician about any underlying renal disease [see Warnings and Precautions (5.4)].

Embryo-Fetal Toxicity
Advise pregnant women of the potential risk to a fetus [see Warnings and Precautions (5.6) and Use in Specific Populations (8.1)].

Advise females of reproductive potential to use effective contraception during treatment with VIDAZA and for 6 months after the last dose. Advise males with female partners of reproductive potential to use effective contraception during treatment with VIDAZA and for 3 months after the last dose. Advise patients to report known or suspected pregnancy to their physicians immediately [see Warnings and Precautions (5.6) and Use in Specific Populations (8.3)].

Lactation
Advise patients to avoid breastfeeding while receiving VIDAZA and for 1 week after the last dose [see Use in Specific Populations (8.2)].

Infertility

Advise males and females that VIDAZA may impair fertility [see Use in Specific Populations (8.3) and Nonclinical Toxicology (13.1)].

Marketed by: | Bristol-Myers Squibb Company
 | Princeton, NJ 08543 USA

VIDAZA® is a trademark of Celgene Corporation, a Bristol-Myers Squibb company.
VIDPI.19

PACKAGE LABEL

Package Label - Principal Display Panel - 100 mg Vial Label

PACKAGE LABEL

Package Label - Principal Display Panel - 100 mg Carton Label